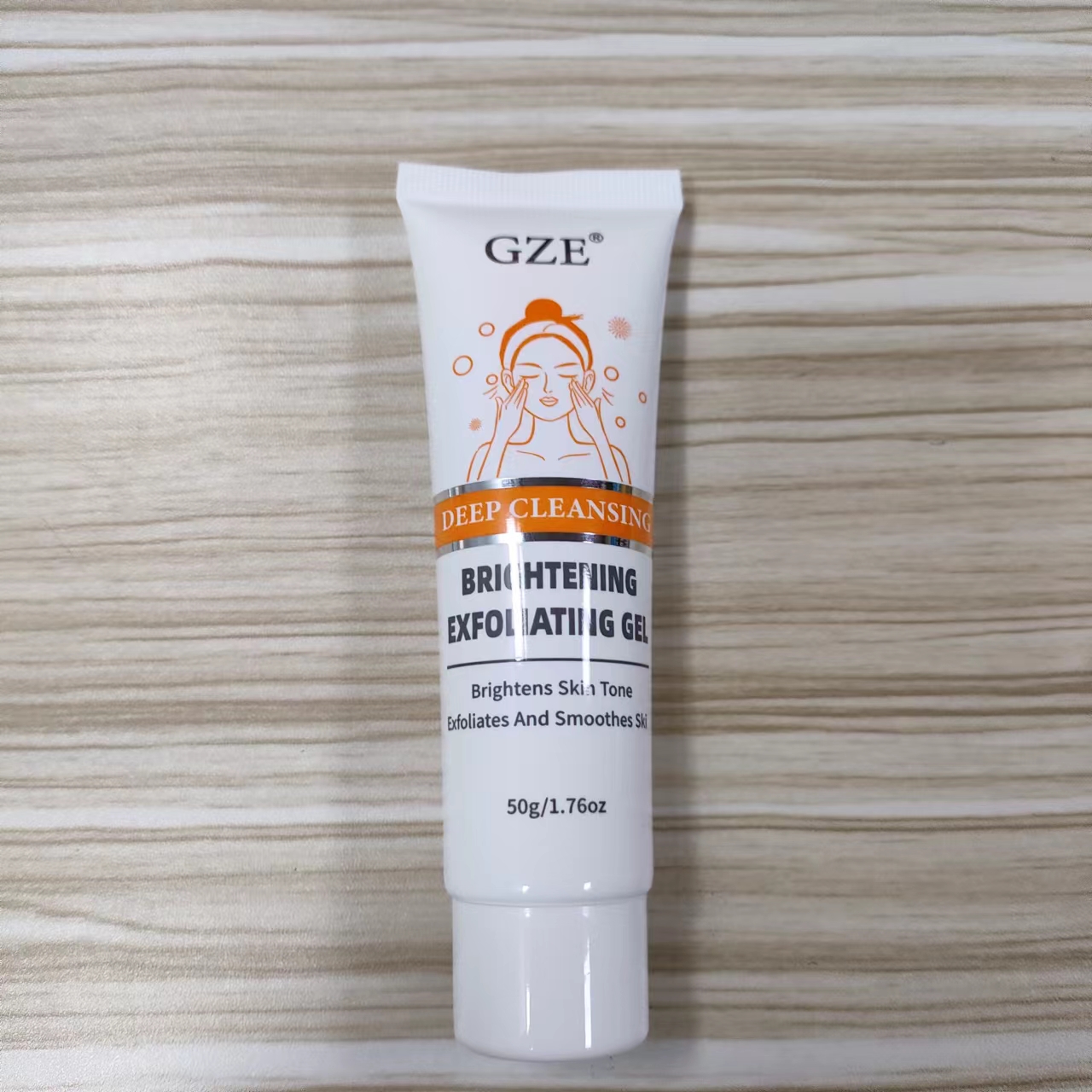 DRUG LABEL: GZE Brightenng Exfoliating Gel
NDC: 74458-037 | Form: GEL
Manufacturer: Guangzhou Yilong Cosmetics Co., Ltd
Category: otc | Type: HUMAN OTC DRUG LABEL
Date: 20241120

ACTIVE INGREDIENTS: ALLANTOIN 0.5 g/100 g; NIACINAMIDE 5 g/100 g
INACTIVE INGREDIENTS: CENTELLA ASIATICA TRITERPENOIDS; HUMAN TYPE I COLLAGEN; ALOE BARBADENSIS LEAF EXTRACT; HAMAMELIS VIRGINIANA (WITCH HAZEL) LEAF EXTRACT; GLYCERIN; TREHALOSE; BUTYLENE GLYCOL; PHENOXYETHANOL; PEG-40 HYDROGENATED CASTOR OIL; AQUA; CARBOMER; ETHYLHEXYLGLYCERIN

GZE BRIGHTENING EXFOLIATING GEL

ACTIVE INGREDIENT

Allantoin

Niacinamide

INACTIVE INGREDIENT

Aqua

Butylene Glycol

Glycerin

Carbomer

Trehalose

Hydrolyzed Collagen

Aloe Barbadensis Leaf Extract

Hamamelis Virginiana (Witch Hazel) Extract

Centella Asiatica Extract

Phenoxyethanol

Ethylhexylglycerin

PEG-40 Hydrogenated Castor Oil

Fragrance

INDICATIONS AND USAGE

After cleansing face, take appropriateproducts
smear on the face. Along the skin texture and gently massagein circular
motions for 1-2 minutes, until thedead skin off the dirt.The rinse with water.

PURPOSE

Exfoliating.

WARNINGS

For external use only.

Stop use and ask a doctor if rash occurs.

Do not use on damaged or broken skin.

When using this product keep out of eyes. Rinse with water to remove.

KEEP OUT OF REACH OF CHILDREN

1. Keep out of reach of children. If swallowed, get medical help or contact a Poison Control Center right away.

DOSAGE AND ADMINISTRATION

After cleansing face, take appropriateproducts
smear on the face. Along the skin texture and gently massagein circular
motions for 1-2 minutes, until thedead skin off the dirt.The rinse with water.